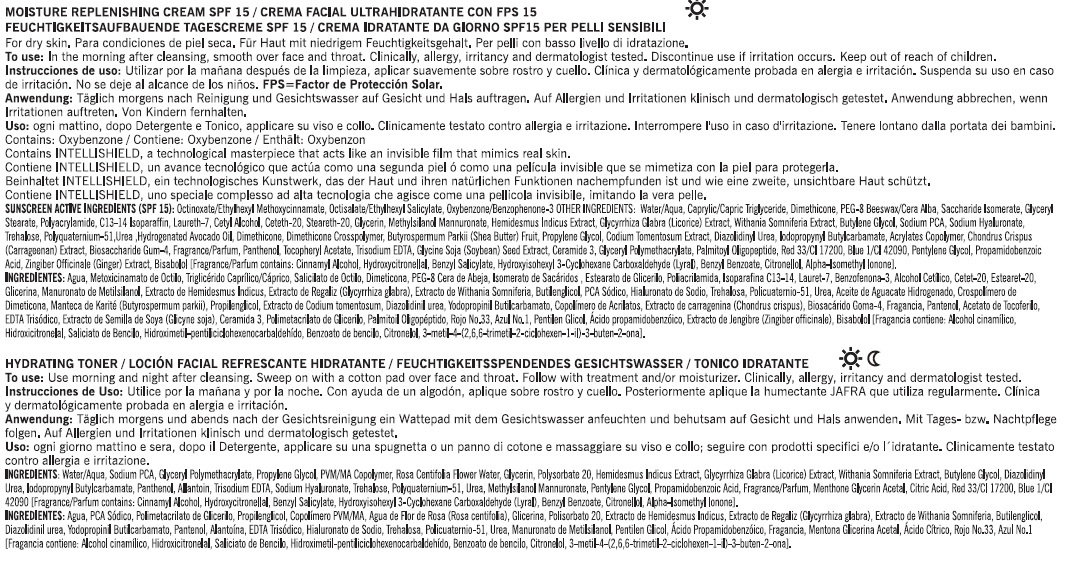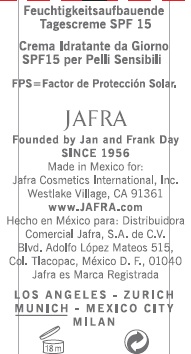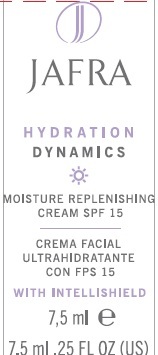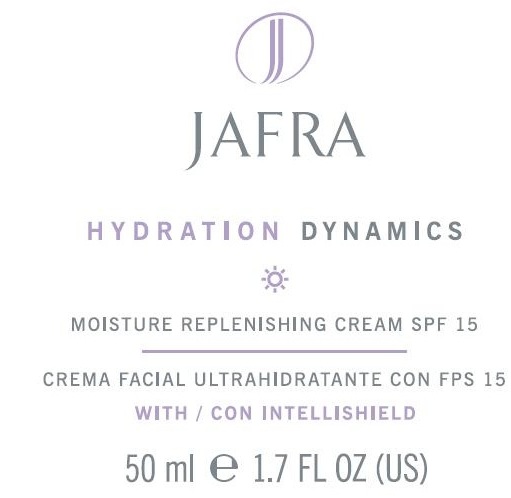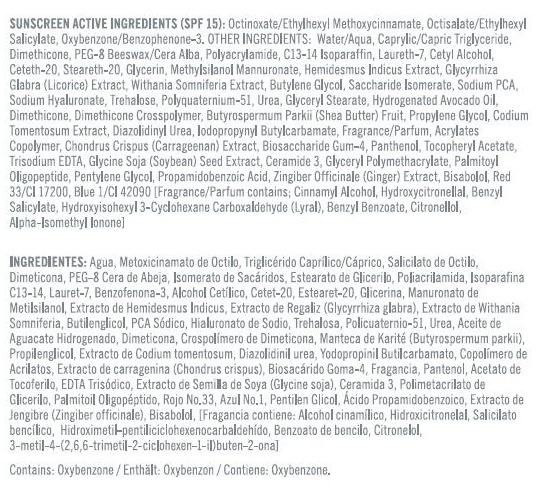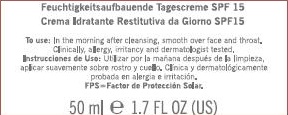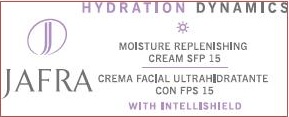 DRUG LABEL: HYDRATION DYNAMICS MOISTURE REPLENISHMENT
NDC: 68828-156 | Form: CREAM
Manufacturer: JAFRA COSMETICS INTERNATIONAL
Category: otc | Type: HUMAN OTC DRUG LABEL
Date: 20120531

ACTIVE INGREDIENTS: OCTINOXATE 6.5 g/100 mL; OCTISALATE 4 g/100 mL; OXYBENZONE 2 g/100 mL
INACTIVE INGREDIENTS: WATER; MEDIUM-CHAIN TRIGLYCERIDES; DIMETHICONE; POLYETHYLENE GLYCOL 400; POLYACRYLAMIDE (10000 MW); C13-14 ISOPARAFFIN; SACCHARIDE ISOMERATE; LAURETH-7; CETYL ALCOHOL; CETETH-20; STEARETH-20; HEMIDESMUS INDICUS ROOT; BIOSACCHARIDE GUM-1; PHYLLANTHUS EMBLICA FRUIT; GLYCYRRHIZA GLABRA; IODOPROPYNYL BUTYLCARBAMATE; DMDM HYDANTOIN; SHEA BUTTER; CHONDRUS CRISPUS; PANTHENOL; .ALPHA.-TOCOPHEROL ACETATE; PENTYLENE GLYCOL; HYDROXYPHENYL PROPAMIDOBENZOIC ACID; PEG-4 LAURATE; GLYCERIN; METHYLSILANOL ASCORBATE; WITHANIA SOMNIFERA FLOWER; BUTYLENE GLYCOL; SODIUM PYRROLIDONE CARBOXYLATE; HYALURONATE SODIUM; TREHALOSE; POLIDRONIUM CHLORIDE; UREA; GLYCERYL MONOSTEARATE; AVOCADO OIL; PROPYLENE GLYCOL; CODIUM TOMENTOSUM; DIAZOLIDINYL UREA; CARBOMER COPOLYMER TYPE A (ALLYL PENTAERYTHRITOL CROSSLINKED); EDETATE TRISODIUM; SOYBEAN SEED OIL; CERAMIDE 3; GLYCERYL 1-ADIPATE; PALMITOYL OLIGOPEPTIDE; GINGER; LEVOMENOL; D&C RED NO. 33; FD&C BLUE NO. 1

HYDRATION DYNAMICS MOISTURE REPLENISHMENT CREAM SPF-15

SUNSCREEN ACTIVE INGREDIENT (SPF 15):
OCTINOXATE/ETHYLHEXYL METHOXYCINNAMATE, OCTISALATE/ETHYLHEXYL SALICYLATE, OXYBENZONE/BENZOPHENONE-3

PURPOSE: SUNSCREEN

INACTIVE INGREDIENT

OTHER INGREDIENTS: WATER/AQUA, CAPRYLIC/CAPRIC TRIGLYCERIDE, DIMETHICONE, PEG-8 BEESWAX/CERA ALBA, POLYACRYLAMIDE, C13-14 ISOPARAFFIN, LAURETH-7, CETYL ALCOHOL, CETETH-20, STEARETH-20, GLYCERIN, METHYLSILANOL MANNURONATE, HEMIDESMUS INDICUS EXTRACT, GLYCYRRHIZA GLABRA (LICORICE) EXTRACT, WITHANIA SOMNIFERIA EXTRACT, BUTYLENE GLYCOL, SACCHARIDE ISOMERATE, SODIUM PCA, SODIUM HYALURONATE, TREHALOSE, POLYQUATERNIUM-51, UREA, GLYCERYL STEARATE, HYDROGENATED AVOCADO OIL, DIMETHICONE, DIMETHICONE CROSSPOLYMER, BUTYROSPERMUM PARKII (SHEA BUTTER) FRUIT, PROPYLENE GLYCOL, CODIUM TOMENTOSUM EXTRACT, DIAZOLIDINYL UREA, IODOPROPYNYL BUTYLCARBAMATE, FRAGRANCE/PARFUM, ACRYLATES COPOLYMER, CHONDRUS CRISPUS (CARRAGEENAN) EXTRACT, BIOSACCHARIDE GUM-4, PANTHENOL, TOCOPHERYL ACETATE, TRISODIUM EDTA, GLYCINE SOYA (SOYBEAN) SEED EXTRACT, CERAMIDE 3, GLYCERYL POLYMETHACRYLATE, PALMITOYL OLIGOPEPTIDE, PENTYLENE GLYCOL, PROPAMIDOBENZOIC ACID, ZINGIBER OFFICINALE (GINGER) EXTRACT, BISABOLOL, RED 33/CI 17200, BLUE 1/CI 42090 [FRAGRANCE/PARFUM CONTAINS: CINNAMYL ALCOHOL, HYDROXYCITRONELLAL, BENZYL SALICYLATE, HYDROXYISOHEXYL 3-CYCLOHEXANE CARBOXALDEHYDE (LYRAL), BENZYL BENZOATE, CITRONELLOL, ALPHA-ISOMETHYL IONONE]

INDICATIONS AND USAGE

MOISTURE REPLENISHING CREAM SPF 15

DOSAGE AND ADMINISTRATION

TO USE: IN THE MORNING AFTER CLEANSING, SMOOTH OVER FACE AND THROAT.

WARNINGS

DISCONTINUE USE IF IRRITATION OCCURS.

KEEP OUT OF REACH OF CHILDREN.

PACKAGE LABEL

JAFRA

HYDRATION DYNAMICS

MOISTURE REPLENISHING CREAM SPF 15